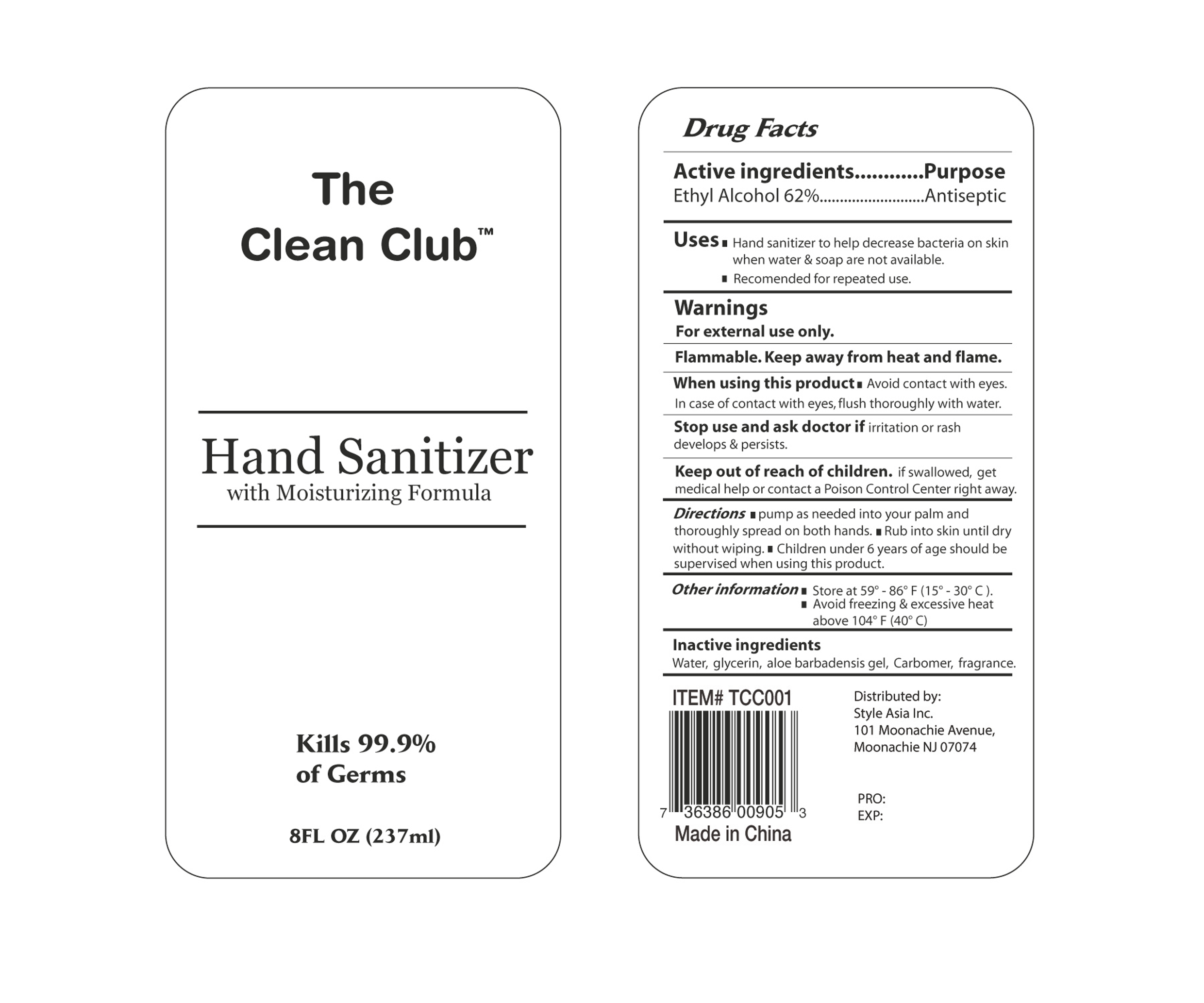 DRUG LABEL: The Clean Club HAND SANITIZER
NDC: 76859-001 | Form: GEL
Manufacturer: Style Asia Inc
Category: otc | Type: HUMAN OTC DRUG LABEL
Date: 20211007

ACTIVE INGREDIENTS: ALCOHOL 62 mL/100 mL
INACTIVE INGREDIENTS: GLYCERIN; WATER; CARBOMER 934; ALOE VERA WHOLE

001

NA

Active Ingredient(s)

Ethyl Alcohol 62% v/v

Purpose

Antiseptic

Use

Hand sanitizer to help decrease bacteria on the skin when water and soap are not available

Recommended for repeated use

Warnings

For external use only.

Flammable,keep away from heat and flame

When using this product keep out of eyes. In case of contact with eyes, flush thoroughly with water.

Stop use and ask a doctor if irritation or rash develops and persists

Keep out of reach of children. If swallowed, get medical help or contact a Poison Control Center right away.

Directions

- Pump as needed into your palm and thoroughly spread on both hands
- Rub into skin until dry without wiping
- Children under 6 years of age should be supervised when using this product

Other Information

Store at 59-86 F (15-30C)

Aviod freezing and ecessive heat above 104F (40C)

Inactive ingredients

Water, glycerin aloe barbadensis gel, carbomer, fragrance.